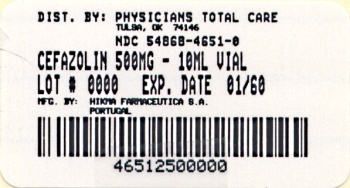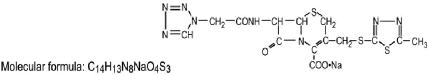 DRUG LABEL: Cefazolin
NDC: 54868-4651 | Form: INJECTION
Manufacturer: Physicians Total Care, Inc.
Category: prescription | Type: HUMAN PRESCRIPTION DRUG LABEL
Date: 20101208

ACTIVE INGREDIENTS: CEFAZOLIN SODIUM 500 mg/10 mL

Rx only

To reduce the development of drug-resistant bacteria and maintain the effectiveness of Cefazolin for Injection, USP and other antibacterial drugs, Cefazolin for Injection, USP should be used only to treat or prevent infections that are proven or strongly suspected to be caused by bacteria.

DESCRIPTION

Cefazolin for Injection, USP, is a sterile semi-synthetic cephalosporin for parenteral administration (Intramuscular or Intravenous). It is the sodium salt of 3-[{(5-methyl -1,3,4 -thiadiazol - 2 - yl) thio]- methyl} - 8 - oxo - 7 - [2 - (1H - tetrazol -1 - yl) acetamido - 5 - thia -1-azabicyclo [4.2.0] oct - 2 - ene - 2 - carboxylic acid. The molecular weight is 476.49.

Cefazolin sodium has the following structural formula:

The sodium content is 48 mg per gram of cefazolin.

Cefazolin for injection, USP is supplied in 500 mg or 1 gram vials for intramuscular or intravenous use and in 1 gram infusion bottles for intravenous use.

Each 500 mg or 1 gram vial contains, cefazolin sodium equivalent to 500 mg or 1 gram of cefazolin. Each 1 gram infusion bottle contains, cefazolin sodium equivalent to 1 gram cefazolin.

CLINICAL PHARMACOLOGY

Human Pharmacology: After intramuscular administration of cefazolin to normal volunteers, the mean serum concentrations were 37 mcg/mL at 1 hour and 3 mcg/mL at 8 hours following a 500 mg dose, and 64 mcg/mL at 1 hour and 7 mcg/mL at 8 hours following a 1 gram dose.

Studies have shown that following intravenous administration of cefazolin to normal volunteers, mean serum concentrations peaked at approximately 185 mcg/mL and were approximately 4 mcg/mL at 8 hours for a 1 gram dose.

The serum half-life for cefazolin is approximately 1.8 hours following IV administration and approximately 2 hours following IM administration.

In a study (using normal volunteers] of constant intravenous infusion with dosages of 3.5 mg/kg for 1 hour (approximately 250 mg) and 1.5 mg/kg the next 2 hours (approximately 100 mg) cefazolin produced a steady serum level at the third hour of approximately 28 mcg/mL.

Studies in patients hospitalized with infections indicate that cefazolin produces mean peak serum levels approximately equivalent to those seen in normal volunteers.

Bile levels in patients without obstructive biliary disease can reach or exceed serum levels by up to five times; however, in patients with obstructive biliary disease, bile levels of cefazolin are considerably lower than serum levels (< 1 mcg/mL).

In synovial fluid, the cefazolin level becomes comparable to that reached in serum at about 4 hours after drug administration. Studies of cord blood show prompt transfer of cefazolin across the placenta. Cefazolin is present in very low concentrations in the milk of nursing mothers.

Cefazolin is excreted unchanged in the urine. In the first 6 hours approximately 60% of the drug is excreted in the urine and this increases to 70% to 80% within 24 hours. Cefazolin achieves peak urine concentrations of approximately 2400 mcg/mL and 4000 mcg/mL respectively following 500 mg and 1 gram intramuscular doses.

In patients undergoing peritoneal dialysis (2 L/hr), cefazolin produced mean serum levels of approximately 10 and 30 mcg/mL after 24 hours' instillation of a dialyzing solution containing 50 mg/L and 150 mg/L respectively. Mean peak levels were 29 mcg/mL (range 13-44 mcg/mL) with 50 mg/L (three patients), and 72 mcg/mL (range 26-142 mcg/mL) with 150 mg/L (six patients). Intraperitoneal administration of cefazolin is usually well tolerated.

Controlled studies on adult normal volunteers, receiving 1 gram 4 times a day for 10 days, monitoring CBC, SGOT, SGPT, bilirubin, alkaline phosphatase, BUN, creatinine and urialysis, indicated no clinically significant changes attributed to cefazolin.

Microbiology: In vitro tests demonstrate that the bactericidal action of cephalosporins results from inhibition of cell wall synthesis.

Cefazolin is active against the following organisms in vitro and in clinical infections:

Staphylococcus aureus (Including penicillinase-producing strains)

Staphylococcus epidermidis

Methicillin-resistant staphylococci are uniformly resistant to cefazolin

Group A beta-hemolytic streptococci and other strains of streptococci (many strains of enterococci are resistant)

Streptococcus pneumoniae

Escherichia coli

Proteus mirabilis

Klebsiella species

Enterobacter aerogenes

Haemophilus influenzae

Most strains of indole positive Proteus (Proteus vulgaris), Enterobacter cloacae, Morganella morganii and Providencia rettgeri are resistant. Serratia, Pseudomonas, Mima, Herellea species are almost uniformly resistant to cefazolin.

Disk Susceptibility Tests

Disk diffusion technique - Quantitative methods that require measurement of zone diameters give the most precise estimates of antibiotic susceptibility. One such procedure1 has been recommended for use with disks to test susceptibility to cefazolin.

Reports from a laboratory using the standardized single-disk susceptibility test1 with a 30 mcg cefazolin disk should be interpreted according to the following criteria:

- Susceptible organisms produce zones of 18 mm or greater, indicating that the tested organism is likely to respond to therapy.
- Organisms of intermediate susceptibility produce zones 15 to 17 mm, indicating that the tested organism would be susceptible if high dosage is used or if the infection is confined to tissues and fluids (e.g., urine), in which high antibiotic levels are attained,
- Resistant organisms produce zones of 14 mm or less, indicating that other therapy should be selected.

For gram-positive isolates, a zone of 18 mm is indicative of a cefazolin-susceptible organism when tested with eitherthe cephalosporin-class disk (30 mcg cephalothin) or the cefazolin disk (30 mcg cefazolin).

Gram-negative organisms should be tested with the cefazolin disk (using the above criteria), since cefazolin has been shown by in vitro tests to have activity against certain strains of enterobacteriaceae found resistant when tested with the cephalothin disk. Gram-negative organisms having zones of less than 18 mm around the cephalothin disk may be susceptible to cefazolin.

Standardized procedures require use of control organisms. The 30 mcg cefazolin disk should give zone diameter between 23 and 29 mm for E. coli ATCC 25922 and between 29 and 35 mm for S. aureus ATCC 25923.

The cefazolin disk should not be used fortesting susceptibility to other cephalosporins.

1Bauer, A.W.;Kirby, W.M.M.; Sherris, J.C., and Turck, M.: Antibiotic Testing by a Standardized Single Disc Method, Am-J. Clin. Path. 45:493, 1966. Standardized Disc Susceptibility Test, Federal Register 39:19182-19184,1974.

Dilution techniques - A bacterial isolate may be considered susceptible if the minimal inhibitory concentration (MIC) for cefazolin is not more than 16 mcg per mL Organisms are considered resistant if the MIC is equal to or greater than 64 mcg per mL.

The range of MIC's for the control strains are as follows:

S. aureus ATCC 25923,0.25 to 1.0 mcg/mL
E. coli ATCC 25922, 1.0 to 4.0 mcg/mL

INDICATIONS AND USAGE

To reduce the development of drug-resistant bacteria and maintain the effectiveness of Cefazolin for Injection, USP and other antibacterial drugs, Cefazolin for Injection, USP should be used only to treat or prevent infections that are proven or strongly suspected to be caused by susceptible bacteria. When culture and susceptibility information are available, they should be considered in selecting or modifying antibacterial therapy. In the absence of such data, local epidemiology and susceptibility patterns may contribute to the empiric selection of therapy.

Cefazolin for injection, USP is indicated in the treatment of the following serious infections due to susceptible organisms:

RESPIRATORY TRACT INFECTIONS due to Streptococcus pneumoniae, Klebsiella species, Haemophilus influenzae, Staphylococcus aureus (penicillin-sensitive and penicillin-resistant) and group A beta-hemolytic streptococci.

Injectable benzathine penicillin is considered to be the drug of choice in treatment and prevention of streptococcal infections including the prophylaxis of rheumatic fever.

Cefazolin is effective in the eradication of streptococci from the nasopharynx; however, data establishing the efficacy of cefazolin in the subsequent prevention of rheumatic fever are not available at present.

URINARY TRACT INFECTIONS due to Escherichia coli, Proteus mirabilis, Klebsiella species and some strains of enterobacter and enterococci.

SKIN AND SKIN STRUCTURE INFECTIONS due to Staphylococcus aureus (penicillin-sensitive and penicillin-resistant), group A beta-hemolytic streptococci and other strains of streptococci.

BILIARY TRACT INFECTIONS due to Escherichia coli, various strains of streptococci, Proteus mirabilis, Klebsiella species and Staphylococcus aureus.

BONE AND JOINT INFECTIONS due to Staphylococcus aureus.

GENITAL INFECTIONS (i.e., prostatitis, epididymitis) due to Escherichia coli, Proteus mirabilis, Klebsiella species and some strains of enterococci.

SEPTICEMIA due to Streptococcus pneumoniae, Staphylococcus aureus (penicillin-sensitive and penicillin-resistant), Proteus mirabilis, Escherichia coli, and Klebsiella species.

ENDOCARDITIS due to Staphylococcus aureus (penicillin-sensitive and penicillin-resistant) and group A beta hemolytic streptococci.

Appropriate culture and susceptibility studies should be performed to determine susceptibility of the causative organism to cefazolin.

PERIOPERATIVE PROPHYLAXIS: The prophylactic administration of cefazolin preoperatively, intraoperatively and postoperatively may reduce the incidence of certain postoperative infections in patients undergoing surgical procedures which are classified as contaminated or potentially contaminated (e.g., vaginal hysterectomy, and cholecystectomy in high-risk patients such as those 70 years of age, with acute cholecystitis, obstructive jaundice or common duct bile stones).

The perioperative use of cefazolin may also be effective in surgical patients in whom infection at the operative site would present a serious risk (e.g., during open-heart surgery and prosthetic arthroplasty).

The prophylactic administration of cefazolin should usually be discontinued within a 24-hour period after the surgical procedure. In surgery where the occurrence of infection may be particularly devastating (e.g., open-heart surgery and prosthetic arthroplasty), the prophylactic administration of cefazolin may be continued for 3 to 5 days following the completion of surgery.

If there are signs of infection, specimens for cultures should be obtained for the identification of the causative organism so the appropriate therapy may be instituted.

(See DOSAGE AND ADMINISTRATION.)

CONTRAINDICATIONS

CEFAZOLIN FOR INJECTION, USP IS CONTRAINDICATED IN PATIENTS WITH KNOWN ALLERGY TO THE CEPHALOSPORIN GROUP OF ANTIBIOTICS.

WARNINGS

BEFORE THERAPY WITH CEFAZOLIN FOR INJECTION, IS INSTITUTED, CAREFUL INQUIRY SHOULD BE MADE TO DETERMINE WHETHER THE PATIENT HAS HAD PREVIOUS HYPERSENSITIVITY REACTIONS TO CEFAZOLIN, CEPHALOSPORINS, PENICILLINS, OR OTHER DRUGS. IF THIS PRODUCT IS GIVEN TO PENICILLIN-SENSITIVE PATIENTS, CAUTION SHOULD BE EXERCISED BECAUSE CROSS-HYPERSENSITIVITY AMONG BETA-LACTAM ANTIBIOTICS HAS BEEN CLEARLY DOCUMENTED AND MAY OCCUR IN UP TO 10% OF PATIENTS WITH A HISTORY OF PENICILLIN ALLERGY. IF AN ALLERGIC REACTION TO CEFAZOLIN FOR INJECTION, USP OCCURS, DISCONTINUE TREATMENT WITH THE DRUG. SERIOUS ACUTE HYPERSENSITIVITY REACTIONS MAY REQUIRE TREATMENT WITH EPINEPHRINE AND OTHER EMERGENCY MEASURES, INCLUDING OXYGEN, IV FLUIDS, IV ANTIHISTAMINES, CORTICOSTEROIDS, PRESSOR AMINES AND AIRWAY MANAGEMENT, AS CLINICALLY INDICATED.

Pseudomembranous colitis has been reported with nearly all antibacterial agents, including cefazolin, and may range in severity from mild to life-threatening. Therefore, it is important to consider this diagnosis in patients who present diarrhea subsequent to the administration of antibacterial agents.

Treatment with antibacterial agents alter the normal flora of the colon and may permit overgrowth of clostridia. Studies indicate that a toxin produced by Clostridium difficile is one primary cause of "antibiotic-associated colitis."

After the diagnosis of pseudomembranous colitis has been established, therapeutic measures should be initiated. Mild cases of pseudomembranous colitis usually respond to drug discontinuation alone. In moderate to severe cases, consideration should be given to management with fluids and electrolytes, protein supplementation and treatment with an antibacterial drug clinically effective against C. difficile colitis.

PRECAUTIONS

General - Prolonged use of Cefazolin for Injection may result in the overgrowth of nonsusceptible organisms. Careful clinical observation of the patient is essential.

Prescribing Cefazolin for Injection, USP in the absence of a proven or strongly suspected bacterial infection or a prophylactic indication is unlikely to provide benefit to the patient and increases the risk of the development of drug-resistant bacteria.

When cefazolin is administered to patients with low urinary output because of impaired renal function, lower daily dosage is required (see DOSAGE AND ADMINISTRATION).

As with other beta-lactam antibiotics, seizures may occur if inappropriately high doses are administered to patients with impaired renal function (see DOSAGE AND ADMINISTRATION).

Cefazolin, as with all cephalosporins, should be prescribed with caution in individuals with a history of gastrointestinal disease, particularly colitis.

Drug Interactions - Probenicid may decrease renal tubular secretion of cephalosporins when used concurrently, resulting in increased and more prolonged cephalosporin blood levels.

Drug/Laboratory Test Interactions - A false positive reaction for glucose in the urine may occur with Benedict's solution, Fehling's solution or with Clinitest® tablets, but not with enzyme-base tests such as Clinistix®.

Positive direct and indirect antiglobulin (Coombs) tests have occurred; these may also occur in neonates whose mothers received cephalosporins before delivery.

Carcinogenesis/Mutagenesis - Mutagenicity studies and long-term studies in animals to determine the carcinogenic potential of Cefazolin for Injection, USP have not been performed.

Pregnancy - Teratogenic Effects - Pregnancy Category B. Reproduction studies have been performed in rats, mice and rabbits at doses up to 25 times the human dose and have revealed no evidence of impaired fertility or harm to the fetus due to cefazolin. There are, however, no adequate and well-controlled studies in pregnant women. Because animal reproduction studies are not always predictive of human response, this drug should be used during pregnancy only if clearly needed.

Labor and Delivery - When cefazolin has been administered prior to caesarian section, drug levels in cord blood have been approximately one quarter to one third of maternal drug levels. The drug appears to have no adverse effect on the fetus.

Nursing Mothers - Cefazolin is present in very low concentrations in the milk of nursing mothers. Caution should be exercised when cefazolin is administered to a nursing woman.

Pediatric Use - Safety and effectiveness for use in prematures, infants and neonates have not been established. See DOSAGE AND ADMINISTRATION for recommended dosage in pediatric patients over 1 month.

Information for Patients - Patients should be counseled that antibacterial drugs including Cefazolin for Injection, USP should only be used to treat bacterial infections. They do not treat viral infections (e.g., the common cold). When Cefazolin for Injection, USP is prescnbed to treat a bacterial infection, patients should be told that although it is common to feel better early in the course of therapy, the medication should be taken exactly as directed. Skipping doses or not completing the full course of therapy may:

(1) decrease the effectiveness of the immediate treatment and

(2) increase the likelihood that bacteria will develop resistance and will not be treatable by Cefazolin for lnjection,USP or other antibacterial drugs in the future.

ADVERSE REACTIONS

The following reactions have been reported:

Gastrointestinal: Diarrhea, oral candidiasis (oral thrush), vomiting, nausea, stomach cramps, anorexia and pseudomembranous colitis. Onset of pseudomembranous colitis symptoms may occur during or after antibiotic treatment (see WARNINGS). Nausea and vomiting have been reported rarely.

Allergic: Anaphylaxis, eosinophilia, itching, drug fever, skin rash, Stevens-Johnson syndrome.

Hematologic: Neutropenia, leukopenia, thrombocytopenia, thrombocythemia.

Hepatic and Renal: Transient rise in SGOT, SGPT, BUN and alkaline phosphatase levels have been observed without clinical evidence of renal or hepatic impairment.

Local Reactions: Rare instances of phlebitis have been reported at the site of injection. Pain at the site of injection after intramuscular administration has occurred infrequently. Some induration has occurred.

Other Reactions: Genital and anal pruritus (including vulvar pruritus, genital moniliasis and vaginitis).

DOSAGE AND ADMINISTRATIONUsual Adult Dosage

Type of infection | Dose | Frequency
Moderate to severe infections | 500 mg to | Every 6 to 8 hours
 | 1 gram
Mild infections caused by susceptible gram | 250 mg to | Every 8 hours
+ cocci | 500 mg
Acute, uncomplicated urinary tract infections | 1 gram | Every 12 hours
Pneumococcal pneumonia | 500 mg | Every 12 hours
Severe, life-threatening infections (e.g., | 1 gram to | Every 6 hours
endocarditis, septicemia)* | 1.5 grams

* In rare instances, doses of up to 12 grams of cefazolin per day have been used.
Perioperative Prophylactic Use

To prevent postoperative infection in contaminated or potentially contaminated surgery, recommended doses are;

1. 1 gram IV or IM administered 1/2 hour to 1 hour prior to the start of surgery.
2. For lengthy operative procedures (e.g., 2 hours or more), 500 mg to 1 gram IV or IM during surgery (administration modified depending on the duration of the operative procedure).
3. 500 mg to 1 gram IV or IM every 6 to 8 hours for 24 hours postoperatively.

It is important that (1) the preoperative dose be given just (1/2 to 1 hour) prior to the start of surgery so that adequate antibiotic levels are present in the serum and tissues at the time of initial surgical incision; and (2) Cefazolin for Injection be administered, if necessary, at appropriate intervals during surgery to provide sufficient levels of the antibiotic at the anticipated moments of greatest exposure to infective organisms.

In surgery where the occurrence of infection may be particularly devastating (e.g., open-heart surgery and prosthetic arthroplasty), the prophylactic administration of Cefazolin for Injection may be continued for 3 to 5 days following the completion of the surgery.

Dosage Adjustment for Patients with Reduced Renal Function

Cefazolin for Injection may be used in patients with reduced renal function with the following dosage adjustments: Patients with a creatinine clearance of 55 mL/min. or greater or a serum creatinine of 1.5 mg % or less can be given full doses, Patients with creatinine clearance rates of 35 to 54 mL/min. or serum creatinine of 1.6 to 3.0 mg % can also be given full doses but dosage should be restricted to at least 8 hour intervals. Patients with creatinine clearance rates of 11 to 34 mL/min. or serum creatinine of 3.1 to 4.5 mg % should be given 1/2 the usual dose every 12 hours. Patients with creatinine clearance rates of 10 mL/min. or less or serum creatinine of 4.6 mg % or greater should be given 1/2 the usual dose every 18 to 24 hours.

All reduced dosage recommendations apply after an initial loading dose appropriate to the severity of the infection. Patients undergoing peritoneal dialysis; See Human Pharmacology.

Pediatric Dosage

In pediatric patients, a total daily dosage of 25 to 50 mg per kg (approximately 10 to 20 mg per pound) of body weight, divided into three or four equal doses, is effective for most mild to moderately severe infections. Total daily dosage may be increased to 100 mg per kg (45 mg per pound) of body weight for severe infections. Since safety for use in premature infants and in neonates has not been established, the use of cefazolin in these patients is not recommended.

Pediatric Dosage Guide
 | 25 mg/kg/day divided | 25 mg/kg/day divided
Weight | into 3 doses | into 4 doses
 |  |  | Vol. (mL) |  | Vol. (mL)
 |  | Approximate | needed with | Approximate | needed with
 |  | single dose | dilution of | single dose | dilution of
Lbs | Kg | mg/q8h | 125 mg/mL | mg/q6h | 125 mg/mL
10 | 4.5 | 40 mg | 0.35 mL | 30 mg | 0.25 mL
20 | 9.0 | 75 mg | 0.60 mL | 55 mg | 0.45 mL
30 | 13.6 | 115 mg | 0.90 mL | 85 mg | 0.70 mL
40 | 18.1 | 150 mg | 1.20 mL | 115 mg | 0.90 mL
50 | 22.7 | 190 mg | 1.50 mL | 140 mg | 1.10 mL

 | 50 mg/kg/day divided | 50 mg/kg/day divided
Weight | into 3 doses | into 4 doses
 |  |  | Vol. (mL) |  | Vol. (mL)
 |  | Approximate | needed with | Approximate | needed with
 |  | single dose | dilution of | single dose | dilution of
Lbs | Kg | mg/q8h | 225 mg/rnL | mg/q6h | 225 mg/mL
10 | 4.5 | 75 mg | 0.35 mL | 55 mg | 0.25 mL
20 | 9.0 | 150 mg | 0.70 mL | 110 mg | 0.50 mL
30 | 13.6 | 225 mg | 1.00 mL | 170 mg | 0.75 mL
40 | 18.1 | 300 mg | 1.35 mL | 225 mg | 1.00 mL
50 | 22.7 | 375 mg | 1.70 mL | 265 mg | 1.25 mL

In pediatric patients with mild to moderate renal impairment (creatinine clearance of 70 to 40 mL/min,), 60 percent of the normal daily dose given in equally divided doses every 12 hours should be sufficient. In patients with moderate impairment (creatinine clearance of 40 to 20 mL/min.), 25 percent of the normal daily dose given in equally divided doses every 12 hours should be adequate. Pediatric patients with severe renal impairment (creatinine clearance of 20 to 5 mL/min.) may be given 10 percent of the normal daily dose every 24 hours. All dosage recommendations apply after an initial loading dose.

RECONSTITITION

Preparation of Parenteral Solution

Parenteral drug products should be SHAKEN WELL when reconstituted, and inspected visually for particulate matter prior to administration. If particulate matter is evident in reconstituted fluids, the drug solutions should be discarded.

When reconstituted or diluted according to the instructions below, Cefazolin is stable for 24 hours at room temperature or for 10 days if stored under refrigeration (5°C or 41°F). Reconstituted solutions may range in color from pale yellow to yellow without a change in potency.

Single dose vials

For IM injection, IV direct (bolus) injection or IV infusion, reconstitute with Sterile Water for Injection according to the following table. SHAKE WELL.

 |  | Approximate | Approximate
Vial size | Amount of diluent | concentration | Available volume
500 mg | 2 mL | 225 mg/mL | 2.2 mL
1 gram | 2.5 mL | 330 mg/mL | 3 mL

Infusion bottles

Reconstitute with 50 to 100 mL of Sodium Chloride Injection or other IV solution listed under ADMINISTRATION. When adding diluent to vial, allow air to escape by using a small vent needle or by pumping the syringe. SHAKE WELL. Administer with primary IV fluids, as a single dose.

ADMINISTRATION

Intramuscular Administration - Reconstitute vials with Sterile Water for Injection according to the dilution table above. Shake well until dissolved. Cefazolin should be injected into a large muscle mass. Pain on injection is infrequent with cefazolin.

Intravenous Administration - Direct (bolus) injection: Following reconstitution according to the above table, further dilute vials with approximately 5 mL Sterile Water for Injection. Inject the solution slowly over 3 to 5 minutes, directly or through tubing for patients receiving parenteral fluids (see list below).

Intermittent or continuous infusion: Dilute reconstituted cefazolin in 50 to 100 mL of one of the following solutions:

- Sodium Chloride Injection, USP
- 5% or 10% Dextrose Injection, USP
- 5% Dextrose in Lactated Ringer's Injection, USP
- 5% Dextrose and 0.9% Sodium Chloride Injection, USP
- 5% Dextrose and 0.45% Sodium Chloride Injection, USP
- 5% Dextrose and 0.2% Sodium Chloride Injection, USP
- Lactated Ringer's Injection, USP
- Invert Sugar 5% or 10% in Sterile Water for Injection
- Ringer's Injection, USP
- 5% Sodium Bicarbonate Injection, USP

HOW SUPPLIED

Cefazolin for Injection, USP, is supplied in vials containing cefazolin sodium equivalent to 500 mg or 1 gram cefazolin and in infusion bottles containing cefazolin sodium equivalent to 1 gram cefazolin:

NDC 54868-4651-0 500mg / 10mL vial, Carton of 25 vials

As with other cephalosporins, Cefazolin for Injection, USP, tends to darken depending on storage conditions; within the stated recommendations, however, product potency is not adversely affected. Before reconstitution, protect from light and store at 20°-25°C (68° - 77°F), [see USP Controlled Room Temperature].

Manufactured by:
Hikma Farmaceutica (Portugal), Lda.
2705-906 Terrugem SNT – PORTUGAL

For:
West-Ward Pharmaceutical Corp.
465 Industrial Way West
EATONTOWN, NJ 07724
USA

Rev. Jan. 2006
PIN001-WES/2

Relabeling of "Additional Barcode Label" by:
Physicians Total Care, Inc.
Tulsa, OK 74146

PRINCIPAL DISPLAY PANEL

Cefazolin for Injection, USP

500 mg/10 mL vial, Carton of 25 vials